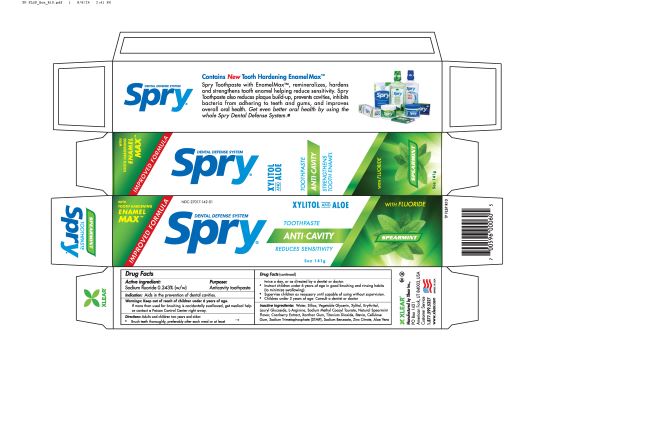 DRUG LABEL: Spry Dentifrice
NDC: 27017-142 | Form: PASTE, DENTIFRICE
Manufacturer: Xlear Inc.
Category: otc | Type: HUMAN OTC DRUG LABEL
Date: 20251111

ACTIVE INGREDIENTS: SODIUM FLUORIDE 2.43 mg/1 g
INACTIVE INGREDIENTS: ZINC CITRATE; ALOE VERA LEAF; CELLULOSE GUM; GLYCERIN; STEVIA LEAF; ERYTHRITOL; LAURYL GLUCOSIDE; SODIUM METHYL COCOYL TAURATE; WATER; SODIUM BENZOATE; TITANIUM DIOXIDE; N2-(4-FLUOROBENZOYL)-L-ARGININE; SPEARMINT OIL; XANTHAN GUM; SODIUM TRIMETAPHOSPHATE; SILICON DIOXIDE; XYLITOL; CRANBERRY

Spry Fluoride Toothpaste

KEEP OUT OF REACH OF CHILDREN

Warning: keep out of reach of children under 6 years of age.

WARNINGS AND PRECAUTIONS

Warnings: If more than used for brushing is accidentaly swallowed, get medical help or contact poison control center right away.

STOP USE

Brush teeth thoroughly, preferably after each meal or at least twice a day, or as directed by a dentist or doctor.

INDICATIONS AND USAGE

Directions: Adults and children two years and older:

Brush teeth thoroughly, preferably after each meal or at least twice a day, or as directed by a dentist or doctor.

Instruct children under 6 years of age in good brushing and rinsing habits (to minimize swallowing).

Supervise children as necessary until capable of using without supervision.

Children under 2 years of age: consult a dentist or doctor.

WARNINGS

Warnings: Keep out of reach of children under 6 years of age.

If more than used for brushing is accidentally swallowed, get medical help or contact poison control center right away

ACTIVE INGREDIENT

Sodium fluoride 0.243% (w/w)

Anticavity toothpaste

PURPOSE

Aids in the prevention of dental cavities

Anticavity Toothpaste

DOSAGE AND ADMINISTRATION

Directions: adults and children two years and older:

brush teeth thoroughly, preferably after each meal or at least twice a day, or as directed by a dentist or doctor.

INACTIVE INGREDIENT

Water, silica, vegetable glycerin, xylitol, erythritol, lauryl glucoside, L-arginine, sodium methyl cocoyl taurate, natural speramint flavor, cranberry extract, xanthan gum, titanium dioxide, stevia, cellulose gum, sodium trimetaphosphate, sodium benzoate, zinc citrate, aloe vera